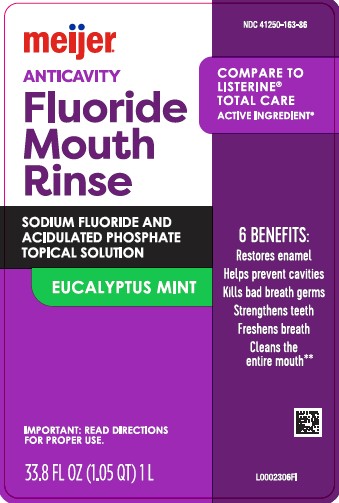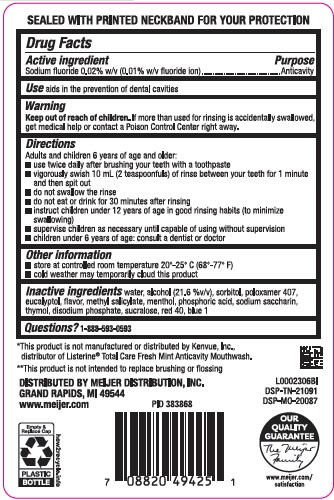 DRUG LABEL: Anticavity
NDC: 41250-163 | Form: MOUTHWASH
Manufacturer: Meijer, Inc.
Category: otc | Type: HUMAN OTC DRUG LABEL
Date: 20260219

ACTIVE INGREDIENTS: SODIUM FLUORIDE 0.2 mg/1 mL
INACTIVE INGREDIENTS: WATER; ALCOHOL; SORBITOL; POLOXAMER 407; EUCALYPTOL; METHYL SALICYLATE; MENTHOL; PHOSPHORIC ACID; SACCHARIN SODIUM; THYMOL; SODIUM PHOSPHATE, DIBASIC, ANHYDROUS; SUCRALOSE; FD&C RED NO. 40; FD&C BLUE NO. 1

Meijer 163.005/163AG
Anticavity Fluoride Rinse

Tamper Evident Statement

SEALED WITH A PRINTED NECKBAND FOR YOUR PROTECTION

Active ingredient

Sodium fluoride 0.02% w/v (0.01% w/v fluoride ion)

Purpose

Anticavity

Use

aids in the prevention of dental cavities

Warning

for this product

Keep out of reach of children.

If more than used for rinsing is accidentally swallowed, get medical help or contact a Poison Control Center right away.

Directions

Adults and children 12 years of age and older:

- use twice daily after brushing your teeth with a toothpaste
- vigorously swish 10 mL (2 teaspoonfuls) of rinse between your teeth for 1 minute then spit out
- do not swallow the rinse
- do not eat or drink for 30 minutes after rinsing
- instruct children under 12 years of age in good rinsing habits (to minimize swallowing)
- supervise children as necessary until capable of using without supervision
- children under 6 years of age: consult a dentist or doctor

Other information

- store at controlled room temperature 20°-25° C to (68° - 77°F)
- cold weather may temporarily cloud this product

Inactive ingredients

water, alcohol (21.6 %v/v), sorbitol, poloxamer 407, eucalyptol, flavor, methyl salicylate, menthol, phosphoric acid, sodium saccharin, thymol, disodium phosphate, sucralose, red 40, blue 1

Questions?

1-888-593-0593

Disclaimers

*This product is not manufactured or distributed by Kenvue, Inc., distributor of Listerine®Total Care Fresh Mint Anticavity Mouthwash.

** This product is not intended to replace brushing or flossing.

Adverse reaction

DISTRIBUTED BY MEIJER DISTRIBUTION, INC

GRAND RAPIDS, MI 49544

www.meijer.com

OUR QUALITY GUARANTEE

The Meijer Family

www.meijer.com/satisfaction

Empty & Replace Cap

PLASTIC BOTTLE

how2recycle.info

Principal panel display

NDC 41250-163-86

meijer®

ANTICAVITY

Fluoride Mouth Rinse

Compare to Listerine®Total Care Active Ingredient*

Sodium Fluoride And Acidulated Phosphate Topical Solution

Eucalyptus Mint

6 Benefits:

Restores enamel

Help prevent cavities

Kills bad breath germs

Strengthens teeth

Freshens Breath

Cleans the entire mouth**

IMPORTANT: Read directions for proper use.

33.8 FL OZ (1.05 QT) 1 L